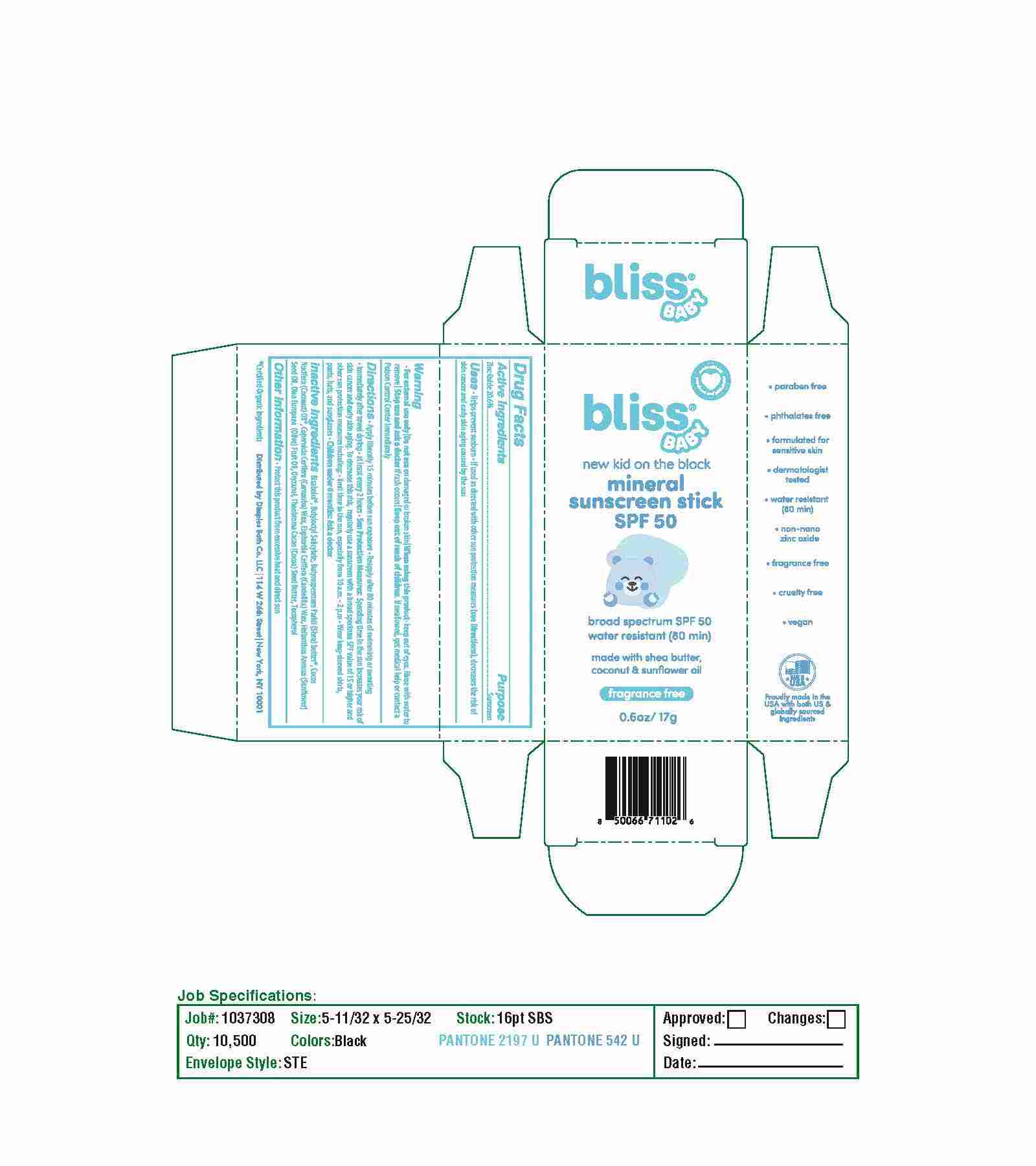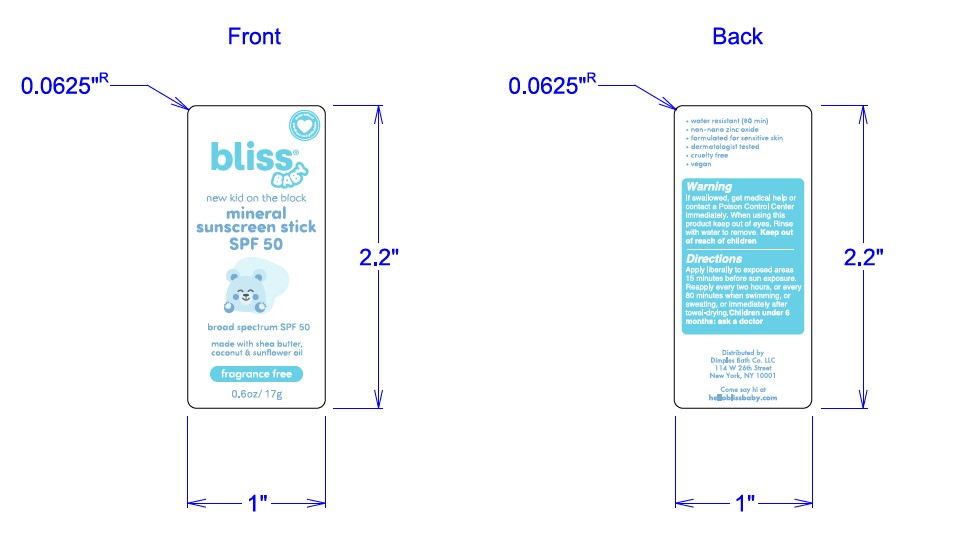 DRUG LABEL: Dimples Bath Co - Sunstick New Kid On The Block
NDC: 84568-550 | Form: STICK
Manufacturer: Dimples Bath Co. LLC
Category: otc | Type: HUMAN OTC DRUG LABEL
Date: 20250106

ACTIVE INGREDIENTS: ZINC OXIDE 21 g/100 g
INACTIVE INGREDIENTS: BISABOLOL 0.3 g/100 g; TOCOPHEROL 0.1425 g/100 g; COCOS NUCIFERA (COCONUT) OIL 23.75 g/100 g; OLEA EUROPAEA (OLIVE) FRUIT OIL 10 g/100 g; EUPHORBIA CERIFERA (CANDELILLA) WAX 14 g/100 g; HELIANTHUS ANNUUS (SUNFLOWER) SEED OIL 18.495 g/100 g; COPERNICIA CERIFERA (CARNAUBA) WAX 2.2 g/100 g; THEOBROMA CACAO (COCOA) SEED BUTTER 2 g/100 g; ORYZANOL 1.5 g/100 g; BUTYROSPERMUM PARKII (SHEA) BUTTER 1.5 g/100 g; BUTYLOCTYL SALICYLATE 5 g/100 g; SQUALENE 0.0375 g/100 g; BETA-SITOSTEROL 0.075 g/100 g

DBC Mineral Stick

ACTIVE INGREDIENT

Zinc Oxide 20.6%

PURPOSE

Sunscreen

Uses

Helps prevent sunburn. If used as directed with other sun protection measures (see Directions), decreases the risk of skin cancer and early skin aging caused by the sun.

WARNINGS

For external use only. Do not use on damaged or broken skin. When using this product keep out of eyes. Rinse with water to remove. Stop use and ask a doctor if rash occurs

Keep out of reach of children. If swallowed, get medical help or contact a Poison Control Center immediately

DOSAGE AND ADMINISTRATION

Directions • Apply liberally 15 minutes before sun exposure • Reapply after 80 minutes of swimming or sweating • Immediately after towel drying at least every 2 hours • Sun Protection Measures Spending time in the sun increases your risk of skin cancer and early skin aging. To decrease this risk, regularly use a sunscreen with a broad spectrum SPF value of 15 or higher and other sun protecting measures including • Limit time in the sun, especially from 1Oam - 2pm Wear long-sleeved shirts, pants, hats, and sunglasses • Children under 6 months Ask a doctor

INACTIVE INGREDIENT

Bisabolol, Butyloctyl Salicylate, Butyrospermum Parkii (Shea) Butter, Cocos Nucifera (Coconut) OiI, Copernicia Cerifera (Carnauba) Wax, Euphorbia Cerifera (Candelilla) Wax, Helianthus Annuus (Sunflower) Seed Oil, Olea Europaea (Olive) Fruit Oil, Oryzanol, Theobroma Cacao (Cocoa) Seed Butter, Tocopherol

OTHER SAFETY INFORMATION

Protect this product from excessive hear and direct sun

QUESTIONS

Come say hi at helloblissbaby.com